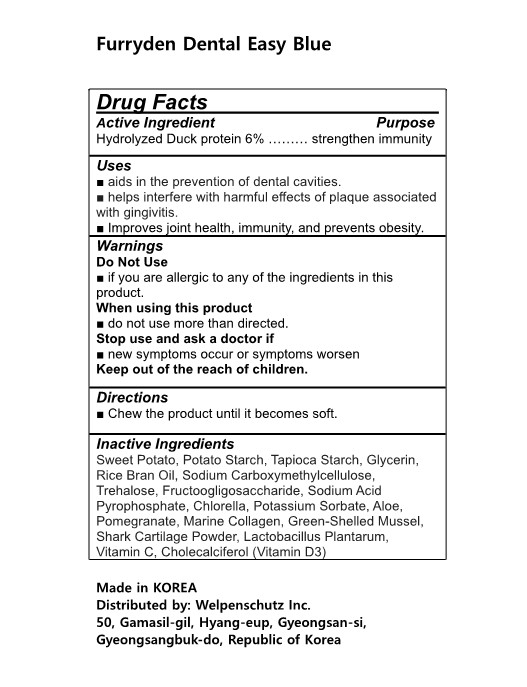 DRUG LABEL: Furryden Dental Easy Blue
NDC: 83332-501 | Form: GUM, CHEWING
Manufacturer: Welpenschutz Inc.
Category: otc | Type: HUMAN OTC DRUG LABEL
Date: 20230209

ACTIVE INGREDIENTS: DUCK 6 g/100 mL
INACTIVE INGREDIENTS: ASCORBIC ACID; HYDROLYSED MARINE COLLAGEN (ENZYMATIC; 2000 MW); STARCH, POTATO; GLYCERIN; RICE BRAN OIL; SODIUM ACID PYROPHOSPHATE; STARCH, TAPIOCA; TREHALOSE; POTASSIUM SORBATE; LACTIPLANTIBACILLUS PLANTARUM; CHOLECALCIFEROL; ALOE; CARBOXYMETHYLCELLULOSE SODIUM; SHARK CARTILAGE; SWEET POTATO; NEW ZEALAND GREEN MUSSEL; FRUCTOSE; CHLORELLA VULGARIS

83332-501 Furryden Dental Easy Blue

Active Ingredients

Hydrolyzed Duck protein 6%

Purposes

Hydrolyzed Duck protein 6% ……… strengthen immunity

Uses

■ aids in the prevention of dental cavities.

■ helps interfere with harmful effects of plaque associated with gingivitis.

■ Improves joint health, immunity, and prevents obesity.

Warnings

Do Not Use

■ if you are allergic to any of the ingredients in this product.

When using this product

■ do not use more than directed.

Stop use and ask a doctor if

■ new symptoms occur or symptoms worsen

Keep out of the reach of children.

Warnings

When using this product

■ do not use more than directed.

Warnings

Stop use and ask a doctor if

■ new symptoms occur or symptoms worsen

Warnings

Keep out of the reach of children.

Warnings

Do Not Use

■ if you are allergic to any of the ingredients in this product.

Directions

■ Chew the product until it becomes soft.

Inactive Ingredients

Sweet Potato, Potato Starch, Tapioca Starch, Glycerin, Rice Bran Oil, Sodium Carboxymethylcellulose, Trehalose, Fructoogligosaccharide, Sodium Acid Pyrophosphate, Chlorella, Potassium Sorbate, Aloe, Pomegranate, Marine Collagen, Green-Shelled Mussel, Shark Cartilage Powder, Lactobacillus Plantarum,

Vitamin C, Cholecalciferol (Vitamin D3)